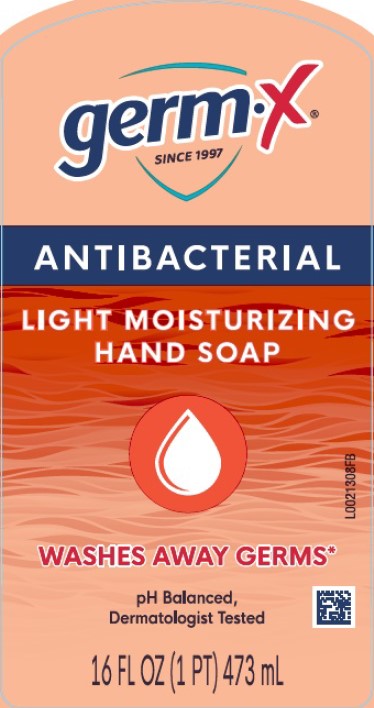 DRUG LABEL: Moisturizing Antibacterial
NDC: 83986-279 | Form: SOAP
Manufacturer: UpLift Brands LLC
Category: otc | Type: HUMAN OTC DRUG LABEL
Date: 20250206

ACTIVE INGREDIENTS: BENZALKONIUM CHLORIDE 1.3 mg/1 mL
INACTIVE INGREDIENTS: WATER; LAURAMINE OXIDE; COCAMIDOPROPYL BETAINE; LAURAMIDOPROPYLAMINE OXIDE; SODIUM CHLORIDE; MYRISTAMIDOPROPYLAMINE OXIDE; GLYCERIN; DISTEARETH-75 ISOPHORONE DIISOCYANATE; PEG-150 DISTEARATE; CITRIC ACID MONOHYDRATE; EDETATE SODIUM; SULISOBENZONE; SODIUM BENZOATE; D&C RED NO. 33; FD&C RED NO. 40; FD&C YELLOW NO. 5

Germ-X 279.003/279.004/279.403/279AD-AE
Light Moisturizing Antibacterial Hand Soap

Claims

ANTIBACTERIAL

HAND SOAP

Active ingredient

Benzalkonium chloride 0.13%

Purpose

Antibacterial

Use

for handwashing to decrease bacteria on the skin

Warnings

For external use only: hands only

When using this product

- avoid contact with eyes. If contact occurs, rinse eyes thoroughly with water

Stop use and ask a doctor if

- irritation or redness develops
- condition persists for more than 72 hours

Keep out of reach of children

If swallowed, get medical help or contact a Poison Control Center right away.

Directions

- wet hands
- apply palmful to hands
- scrub thoroughly
- rinse thoroughly

Inactive ingredients

water, lauramine oxide, cocamidopropyl betaine, lauramidopropylamine oxide, sodium chloride, myristamidopropylamine oxide, glycerin, fragrance, disteareth-75 IPDI, PEG-150 distearate, citric acid, tetrasodium EDTA, benzophenone-4, sodium benzoate, red 33, red 40, yellow 5

Claims

*Washing hands helps wash away bacteria and germs.

Adverse reaction

DISTRIBUTED BY:

UPLIFT BRANDS, LLC

ST. LOUIS, MO 63114

www.germx.com

Principal Display Panel

germ-X®

SINCE 1997

ANTIBACTERIAL

LIGHT MOISTURIZING

HAND SOAP

WASHES AWAY GERMS*

pH Balanced,

Dermatologist Tested

16 FL OZ (1 PT) 473 mL